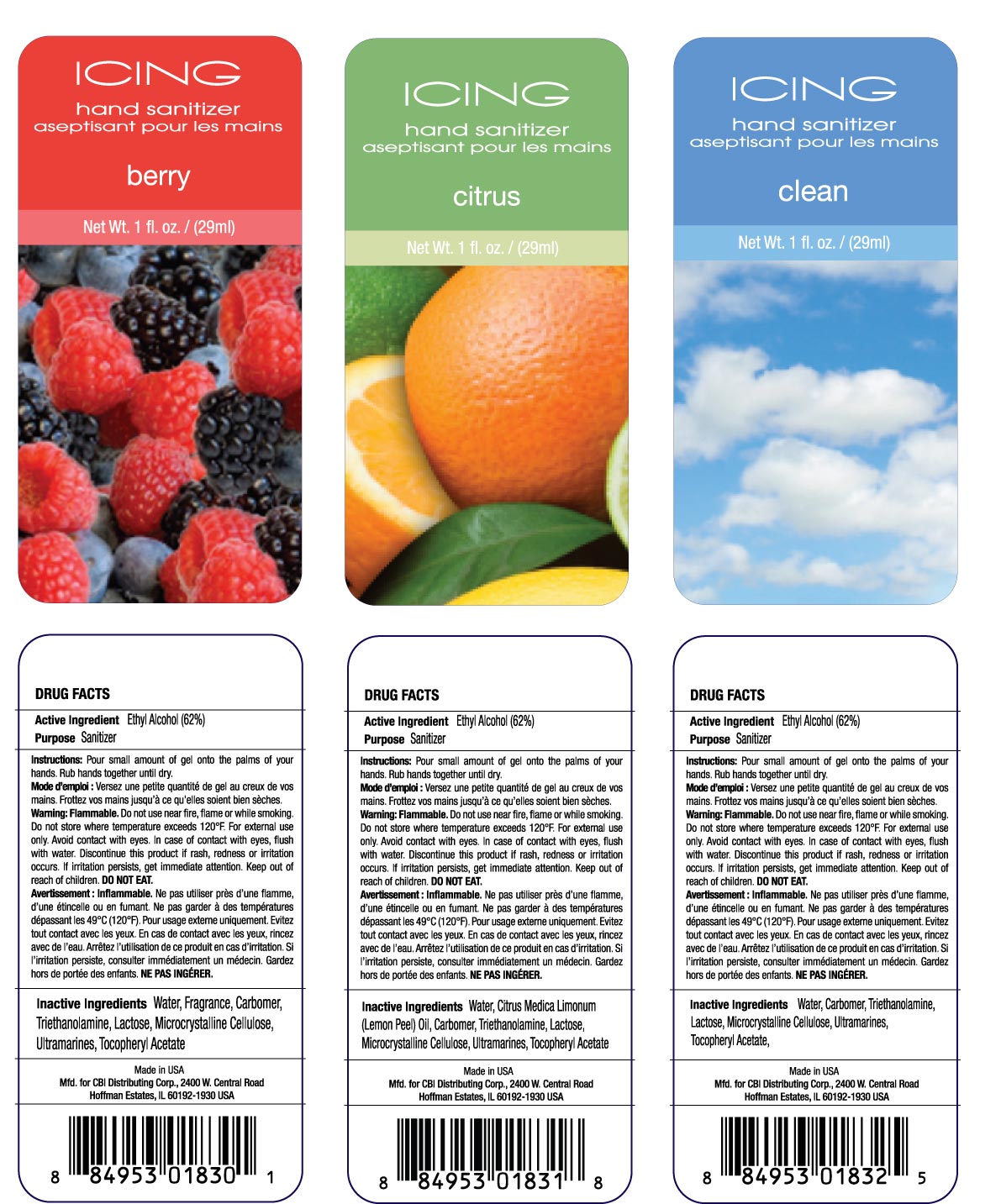 DRUG LABEL: ICING
NDC: 10827-0003 | Form: GEL
Manufacturer: Yusef Manufacturing Laboratories, LLC
Category: otc | Type: HUMAN OTC DRUG LABEL
Date: 20100310

ACTIVE INGREDIENTS: ALCOHOL 0.62 g/1 g
INACTIVE INGREDIENTS: WATER; CARBOMER HOMOPOLYMER TYPE C; TROLAMINE; LACTOSE; CELLULOSE, MICROCRYSTALLINE; FERRIC OXIDE RED; (PHTHALOCYANINATO(2-)) COPPER

Icing Hand Sanitizer - Aseptisant Pour Les Mains (Berry, Citrus, Clean)

Purpose Sanitizer

Instructions: Pour small amount of gel into the palm of your hands. Rub hands together until dry.
Mode d'emploi: Versez une petite quantite de gel au creux de vos mains. Frottez vos mains jusqu'a ce qu'elles soient bien seches.

WARNINGS

Warning: Flammable. Do not use near fire, flame or while smoking. Do not store where temperature exceeds 120 F. For external use only. Avoid contact with eyes. In case of contact with eyes, flush with water. Discontinue this product if rash, redness or irritation occurs. If irritation persists, get immediate attention. Keep out of reach of children. DO NOT EAT.

Advertissement: Inflammable. Ne pas utiliser pres d'une fiamme, d'une etincelle ou en fumant. Ne pas garder a des temperatures depassant les 49 C (120 F). Pour usage exteme uniquement. Evitez tout contact avec les yeux. En cas de contact avec les yeux, rincez avec de l'eau. Arretez l'utilisation de ce produit en cas d'irritation. Si l'irritation persiste, consulter immediatement un medecin. gardez hors de portee des enfants. NE PAS INGERER.

INACTIVE INGREDIENT

Inactive Ingredients Water, Fragrance, Carbomer, Triethanolamine, Lactose, Microcrystalline Cellulose, Ultramarines, Tocopheryl Acetate

Made in USA

CBI Distributing Corp. 2400 W. Central Road
Hoffman Estates, IL 60192-1930 U.S.A.

PACKAGE LABEL

Enter section text here

Active Ingredient Ethyl Alcohol (62%)

Net Wt. 1 fl. oz. / (29ml)